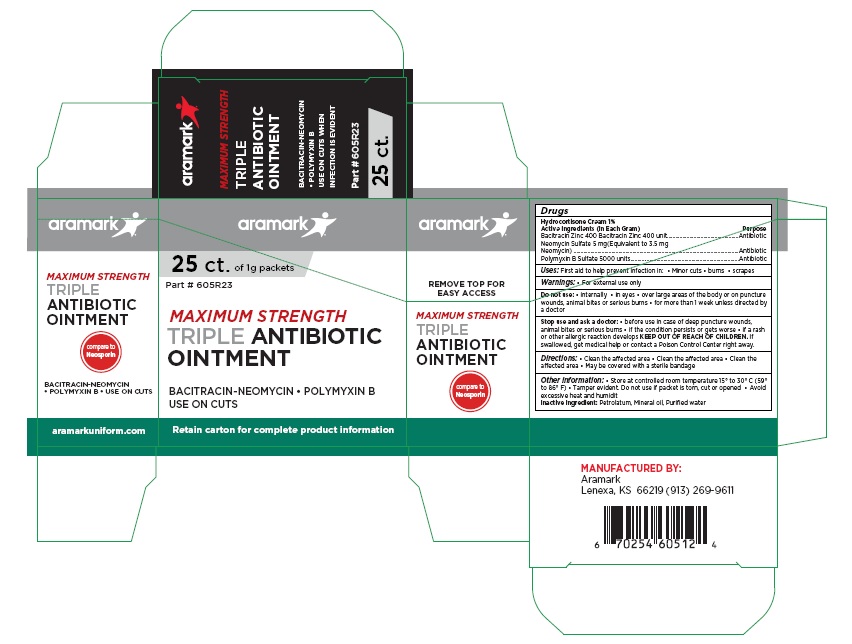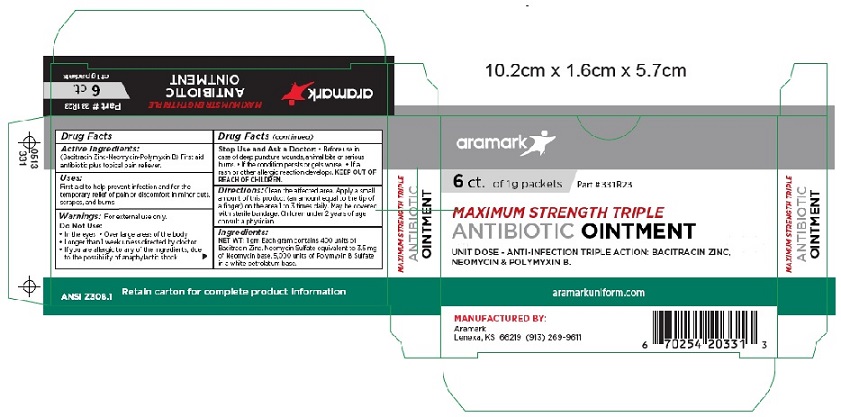 DRUG LABEL: MAXIMUM STRENGTH TRIPLE ANTIBIOTIC
NDC: 81238-4605 | Form: OINTMENT
Manufacturer: Western First Aid Safety dba Aramark
Category: otc | Type: HUMAN OTC DRUG LABEL
Date: 20210521

ACTIVE INGREDIENTS: BACITRACIN ZINC 400 [iU]/1 g; NEOMYCIN SULFATE 3.5 mg/1 g; POLYMYXIN B SULFATE 5000 [iU]/1 g
INACTIVE INGREDIENTS: PETROLATUM; MINERAL OIL; WATER

aramark Maximum Strength Triple Antibiotic Ointment

Drug Facts

Active Ingredients:

(Bacitracin Zinc-Neomycin-Polymyxin B)

PURPOSE

First aid antibiotic plus topical pain reliever.

Uses:

First aid to help prevent infection and for the
temporary relief of pain or discomfort in minor cuts,
scrapes, and burns.

Warnings: For external use only.

Do Not Use:

• In the eyes • Over large areas of the body
• Longer than 1 week unless directed by doctor
• If you are allergic to any of the ingredients,
due to the possibility of anaphylactic shock

Stop Use and Ask a Doctor: • Before use in
case of deep puncture wounds, animal bite or serious
burns. • If the condition perists or gets worse. • If a
rash or other allergic reaction develops.

KEEP OUT OF REACH OF CHILDREN.

DOSAGE AND ADMINISTRATION

Directions: Clean the aff¬ected area. Apply a small
amount of this product (an amount equal to the tip of
a finger) on the area 1 to 3 times daily. May be covered
with sterile bandage. Children under 2 years of age
consult a physician.

OTHER SAFETY INFORMATION

Ingredients:
NET WT: 1 gm Each gram contains 400 units of
Bacitracin Zinc. Neomycin Sulfate equivalent to 3.5 mg
of Neomycin base. 5,000 units of Polymyxin B Sulfate
in a white petrolatum base.

Inactive Ingredients: Petrolatum, Mineral oil, Purified water

Principal Display Panel

aramark

6 ct. of 1g packets

MAXIMUM STRENGTH TRIPLE

ANTIBIOTIC OINTMENT

UNIT DOSE - ANTI-INFECTION TRIPLE ACTION: BACITRACIN ZINC,
NEOMYCIN & POLYMYXIN B.

aramarkuniform.com

MANUFACTURED BY:
Aramark
Lenexa, KS 66219 (913) 269-9611

6 Count

25 Count

res